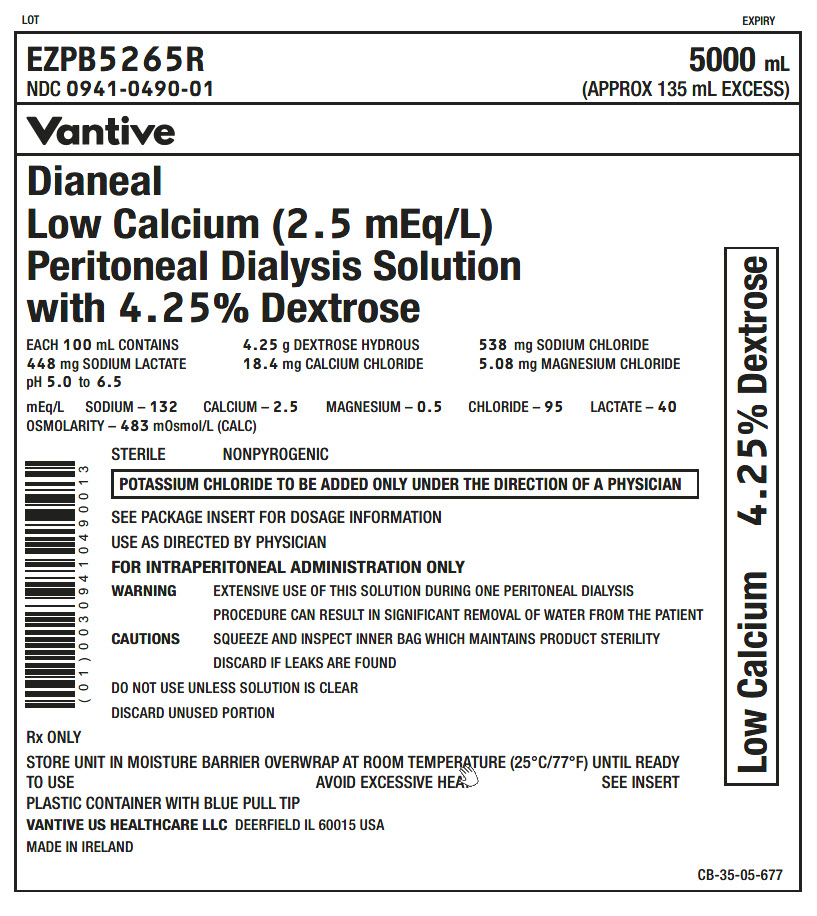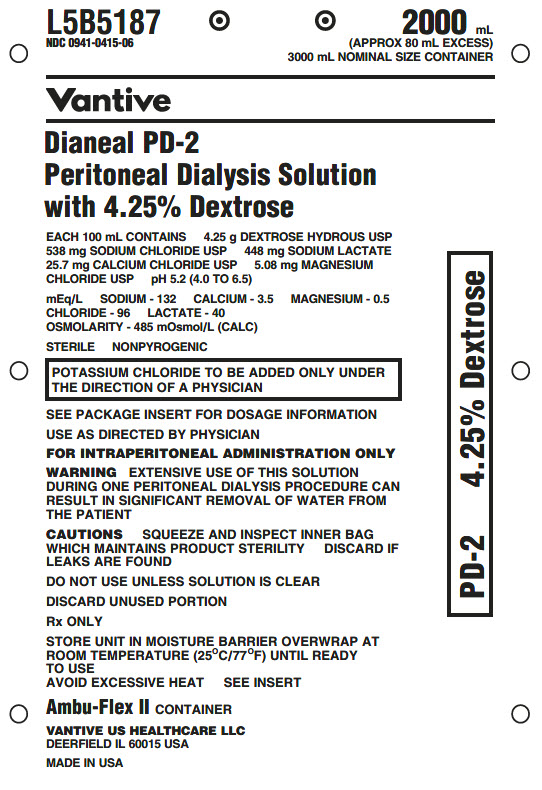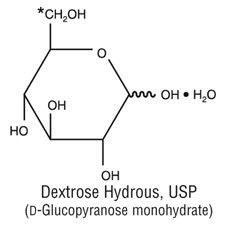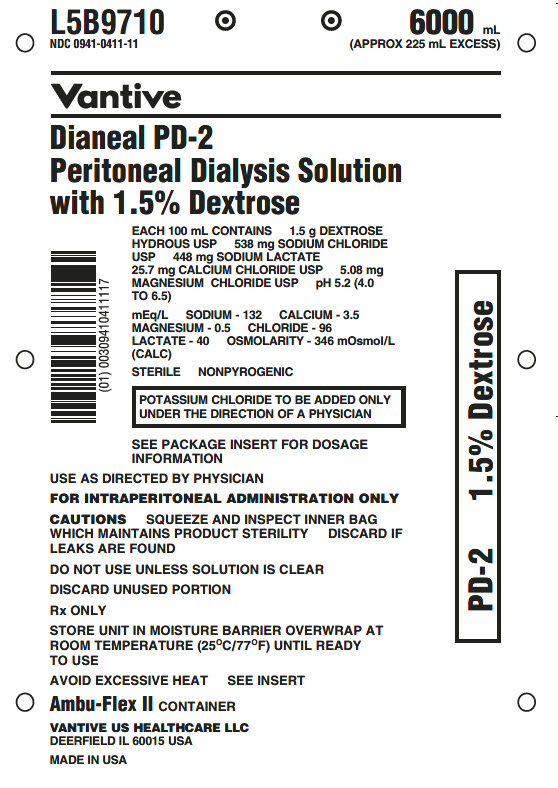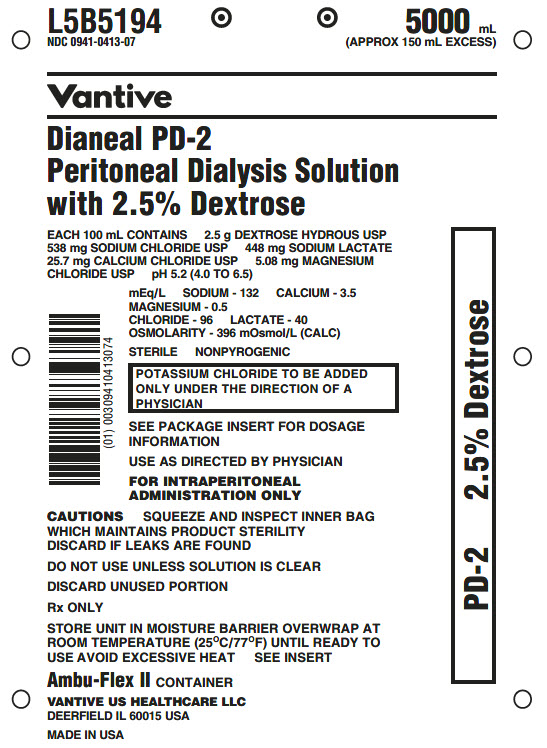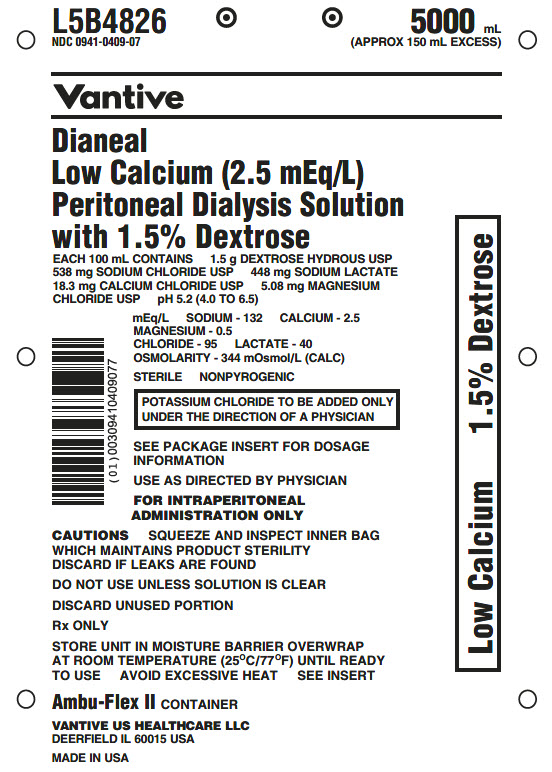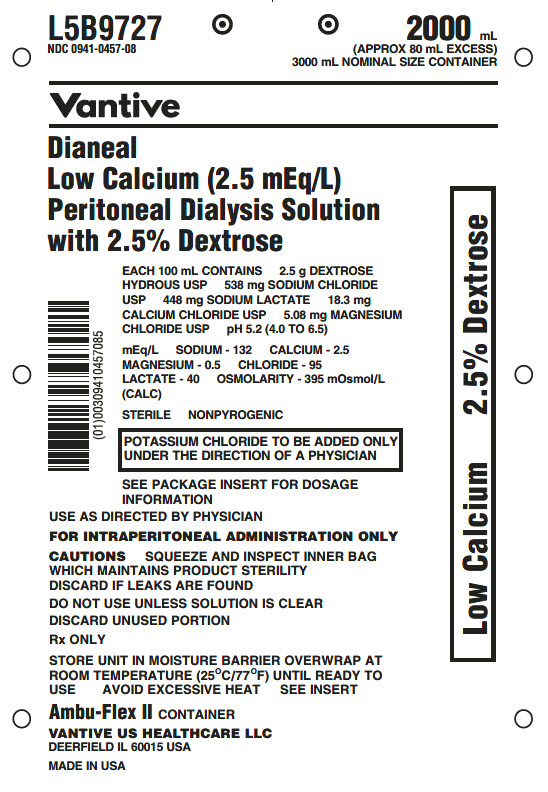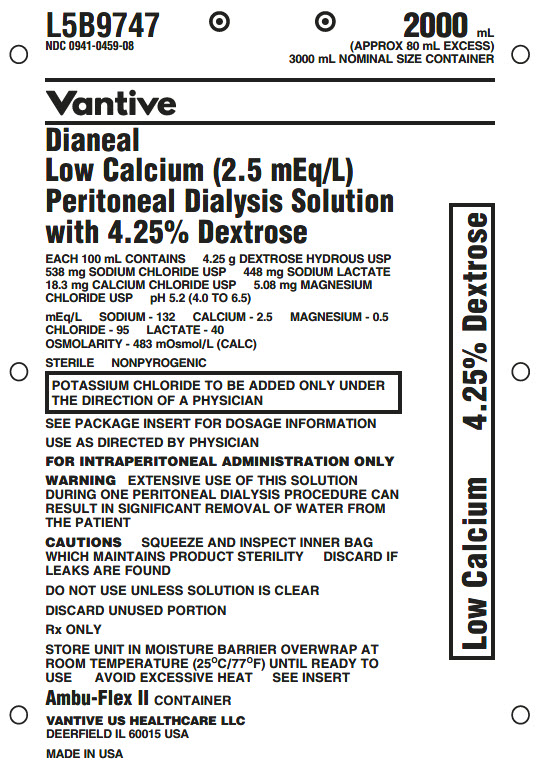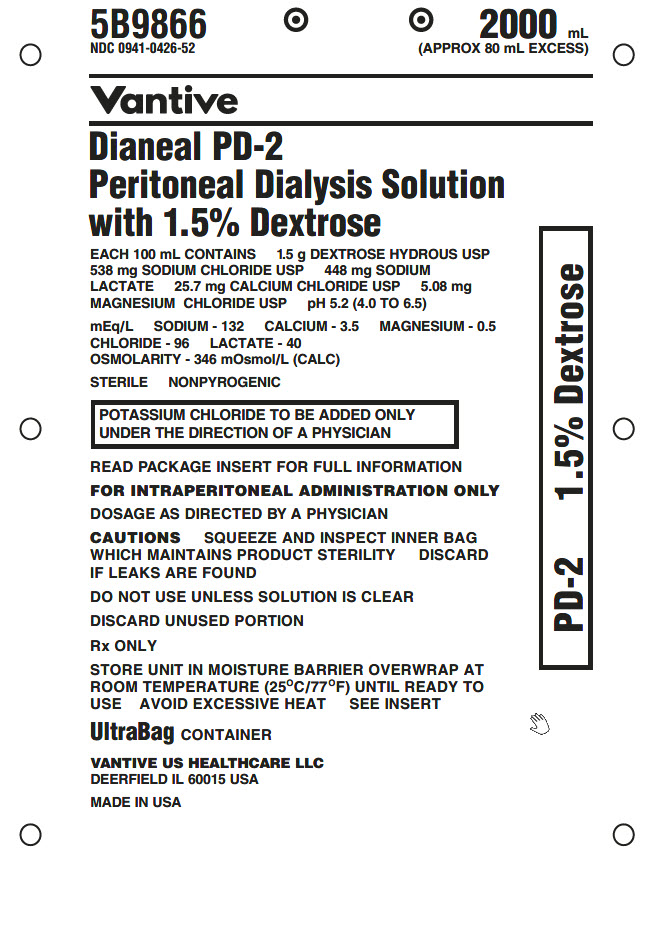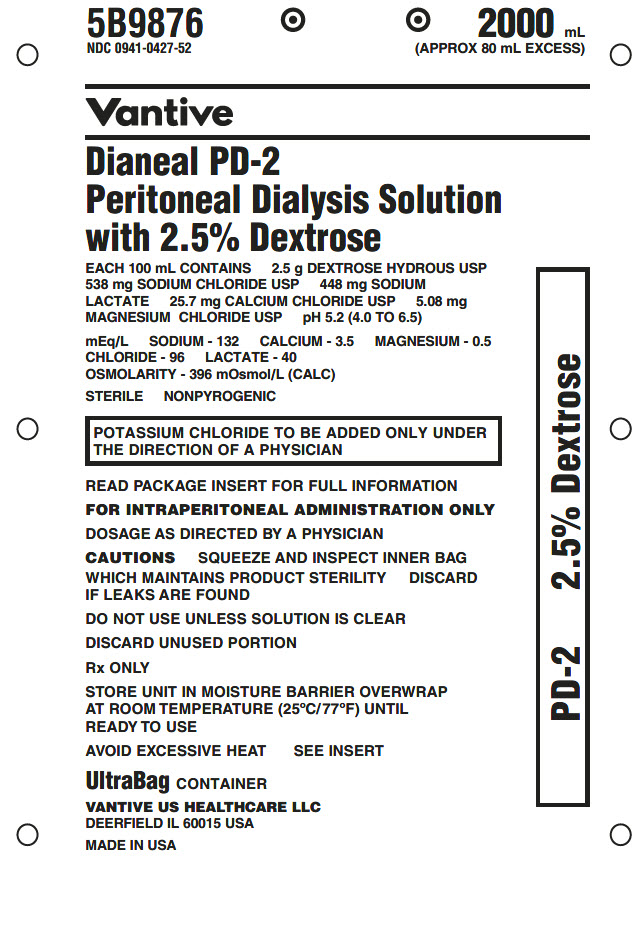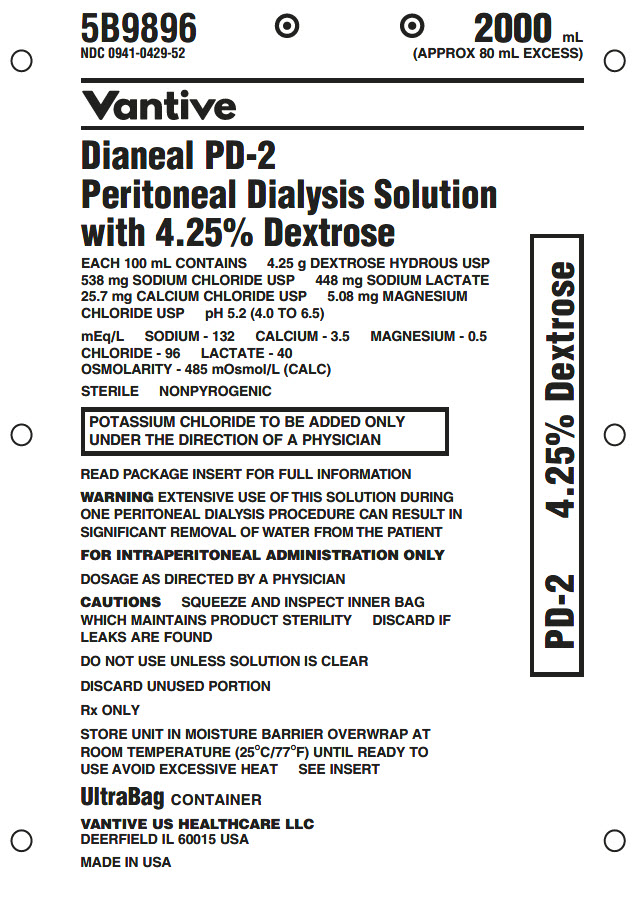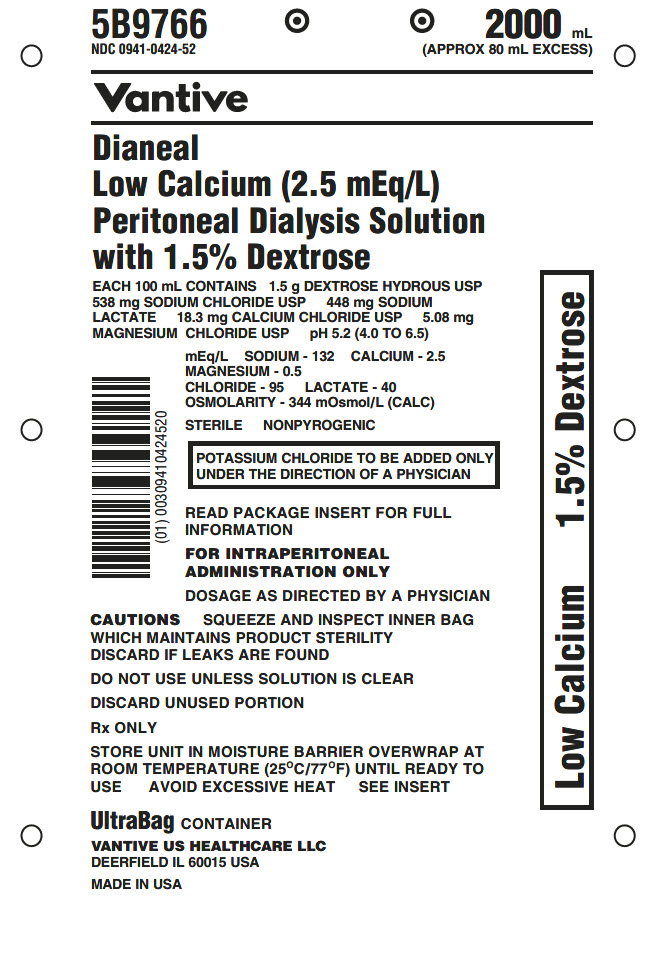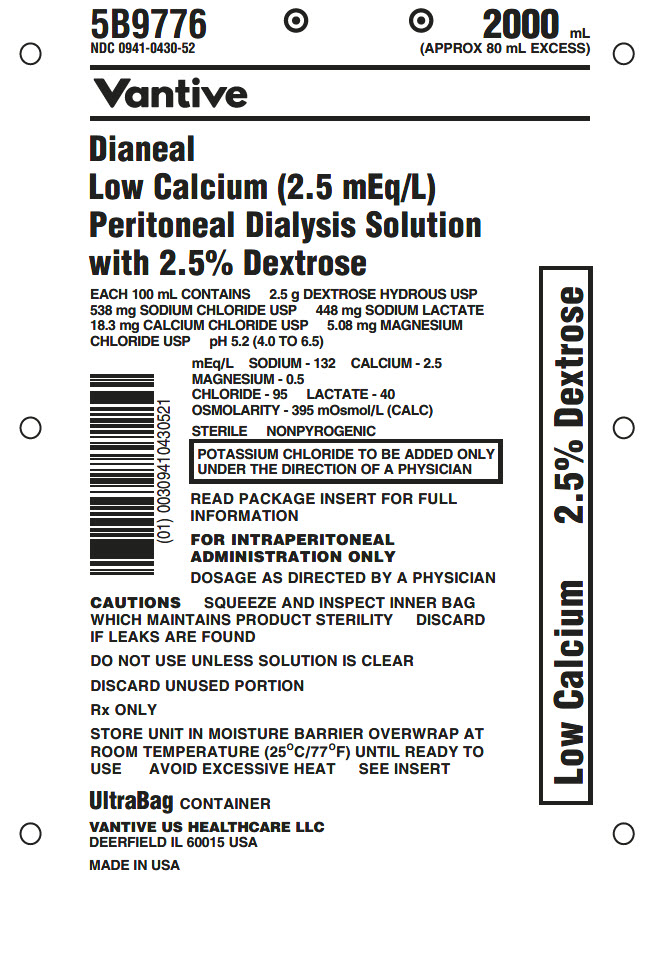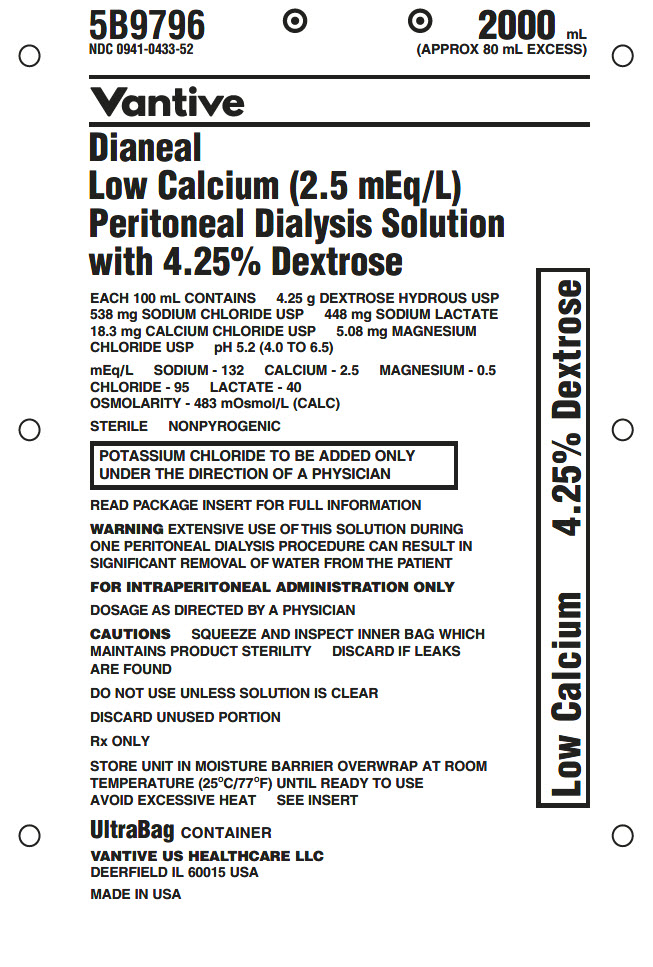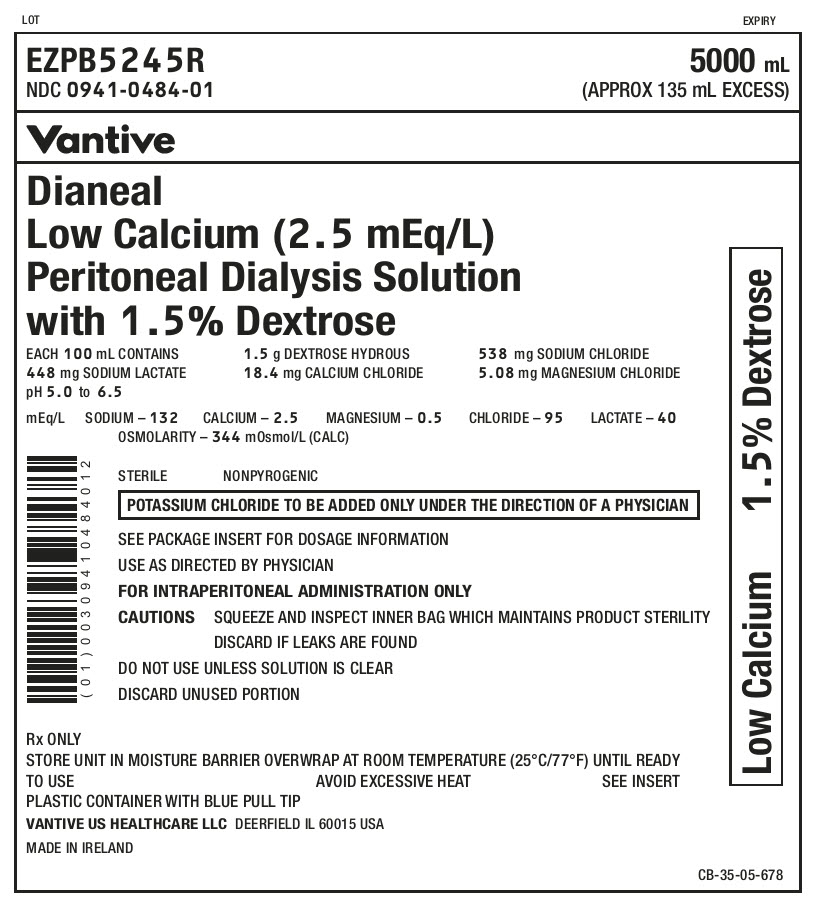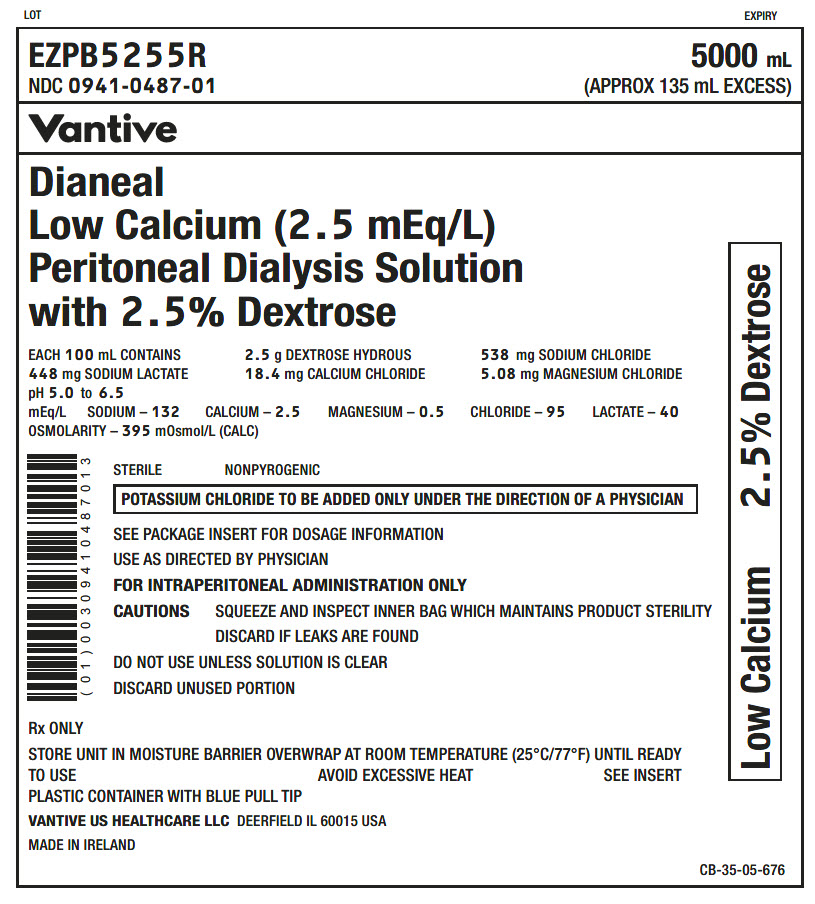 DRUG LABEL: DIANEAL PD-2 with Dextrose
NDC: 0941-0411 | Form: INJECTION, SOLUTION
Manufacturer: Vantive US Healthcare LLC
Category: prescription | Type: HUMAN PRESCRIPTION DRUG LABEL
Date: 20251031

ACTIVE INGREDIENTS: DEXTROSE MONOHYDRATE 1.5 g/100 mL; SODIUM CHLORIDE 538 mg/100 mL; SODIUM LACTATE 448 mg/100 mL; CALCIUM CHLORIDE 25.7 mg/100 mL; MAGNESIUM CHLORIDE 5.08 mg/100 mL
INACTIVE INGREDIENTS: WATER

HIGHLIGHTS OF PRESCRIBING INFORMATION

These highlights do not include all the information needed to use DIANEAL peritoneal dialysis solutions safely and effectively. See full prescribing information for DIANEAL solutions
DIANEAL (dextrose) peritoneal dialysis solution
Initial U.S. Approval: 1981
DIANEAL PD-2 (dextrose) peritoneal dialysis solution
Initial U.S. Approval: 1992
DIANEAL LOW CALCIUM (dextrose) peritoneal dialysis solution
Initial U.S. Approval: 1992

1 INDICATIONS AND USAGE

For management of acute or chronic renal failure.

2 DOSAGE AND ADMINISTRATION

For intraperitoneal administration only. (2)

3 DOSAGE FORMS AND STRENGTHS

DIANEAL solutions are available in multiple combinations of ingredients and in composition, calculated osmolarity, pH, and ionic concentrations. See full prescribing information for detailed descriptions of each formulation. (3)

4 CONTRAINDICATIONS

- Pre-existing severe lactic acidosis (4)

5 WARNINGS AND PRECAUTIONS

- Encapsulating peritoneal sclerosis (5.1)
- Peritonitis: Initiate appropriate antimicrobial therapy (5.1)
- Monitor for lactic acidosis in patients at risk (5.2)
- Monitor for electrolyte, fluid, and nutrition imbalances (5.4)

6 ADVERSE REACTIONS

To report SUSPECTED ADVERSE REACTIONS, contact Vantive US Healthcare LLC at 1-855-857-0003 or FDA at 1-800-FDA-1088 or www.fda.gov/medwatch.

FULL PRESCRIBING INFORMATION

1 INDICATIONS AND USAGE

DIANEAL peritoneal dialysis solutions are indicated for patients in acute or chronic renal failure.

2 DOSAGE AND ADMINISTRATION

2.1 Basic Dosing Information

DIANEAL peritoneal dialysis solutions are intended for intraperitoneal administration only. Not for intravenous or intra-arterial administration..

Select mode of therapy, frequency of treatment, formulation, fill volume, duration of dwell, and length of dialysis based on the patient’s clinical condition, fluid, electrolyte and specific needs. The fill volume depends on body size, usually from 2.0 to 2.5 liters per 1.73m^2 for adults.

DIANEAL peritoneal dialysis solutions are intended for use in Continuous Ambulatory Peritoneal Dialysis (CAPD) or Automated Peritoneal Dialysis (APD). Refer to directions accompanying ancillary equipment for CAPD and APD system preparation.

Product Selection

To avoid the risk of severe dehydration and hypovolemia and to minimize the loss of protein, it is advisable to select the peritoneal dialysis solution with the lowest level of osmolarity consistent with the fluid removal requirements for that exchange. As the patient’s body weight becomes closer to the ideal dry weight, lowering the dextrose concentration of DIANEAL solution is recommended. DIANEAL 4.25% dextrose-containing solution has the highest osmolarity of the DIANEAL solutions and using it for all exchanges may cause dehydration [see Dosage Forms and Strengths (3)].

2.2 Adding Medications

If the resealable rubber plug on the medication port is missing or partly removed, do not use the product if medication is to be added.

To add a medication:

1. Put on mask. Clean and/or disinfect hands.
2. Prepare medication port site using aseptic technique.
3. Using a syringe with a 1-inch long, 25- to 19-gauge needle, puncture the medication port and inject additive.
4. Reposition container with container ports up and evacuate medication port by squeezing and tapping it.
5. Mix solution and additive thoroughly.

2.3 Directions for Use

Warming

DIANEAL peritoneal dialysis solution can be warmed to 37°C (98.6°F). Only dry heat should be used. For CAPD, it is best to warm solutions within the overwrap using a heating pad. Do not immerse DIANEAL solutions in water for warming. Do not use a microwave oven to warm DIANEAL solutions.

To Open

To open, tear the overwrap down at the slit and remove the solution container. Do not use sharp objects to remove the overwrap.

Product Inspection

Parenteral drug products should be inspected visually for particulate matter and discoloration prior to administration. Do not use solutions that are cloudy, discolored, contain visible particulate matter, or show evidence of leakage. Some opacity of the plastic, due to moisture absorption during the sterilization process, may be observed. This does not affect the solution quality or safety and may often leave a slight amount of moisture within the overwrap. The opacity should diminish gradually.

Inspect the bag connector to ensure the tip protector (pull ring or blue pull tip) is attached. Do not use if the tip protector is not attached to the connector. Inspect the DIANEAL solution for signs of leakage and check for minute leaks by squeezing the container firmly. If the container has frangible(s), inspect that they are positioned correctly and are not broken. Do not use DIANEAL solution if the frangible(s) are broken or leaks are suspected as sterility may be impaired.

For DIANEAL solutions in ULTRABAG containers, inspect the tubing and drain container for presence of solution. Small droplets are acceptable, but if solution flows past the frangible prior to use, do not use and discard the units.

CAPD therapy using ULTRABAG containers

Select appropriate formulation from Table 1.

Put on mask. Clean and/or disinfect hands. Using aseptic technique;

1. Uncoil tubing and drain bag, ensuring that the transfer set is closed.
2. Break the connector (Y-set) frangible.
3. Remove the tip protector from connector of solution container. Do not reuse the solution or container once the tip protector is removed.
4. Immediately attach the solution container to patient connector (transfer set).
5. Clamp solution line and then break frangible near solution bag. Hang solution container and place the drainage container below the level of the abdomen.
6. Open transfer set to drain the solution from abdomen. If drainage cannot be established, contact your clinician. When drainage complete, close transfer set.
7. Remove clamp from solution line and flush new solution to flow into the drainage container for 5 seconds to prime the line. Clamp drain line after flush complete.
8. Open transfer set to fill. When fill complete, close transfer set.
9. Disconnect ULTRABAG container from transfer set and apply MINICAP disconnect cap.
10. Upon completion of therapy, discard any unused portion.

APD therapy using AMBU-FLEX containers with pull rings or plastic containers with blue pull tips or pull rings

Select appropriate formulation from Table 1, 2 or 3.

Put on mask. Clean and/or disinfect hands. Using aseptic technique;

1. Remove the tip protector from connector of solution container. Do not reuse the solution or container once the tip protector is removed.
2. Immediately attach the solution container to an appropriate automated peritoneal dialysis set.
3. Continue therapy as instructed in user manual or directions accompanying tubing sets for automated peritoneal dialysis.
4. Upon completion of therapy, discard any unused portion.

3 DOSAGE FORMS AND STRENGTHS

DIANEAL peritoneal dialysis solution is formulated with the following ionic concentrations:

Table 1 - DIANEAL PD-2 and Low Calcium Peritoneal Dialysis Solution ULTRABAG Container for CAPD therapy AMBU-FLEX Container with pull ring for APD therapy
 |  |  | Ionic Concentration (mEq/L)
 | OSMOLARITY (mOsmol/L) (calc) | pH | Sodium | Calcium | Magnesium | Chloride | Lactate
DIANEAL PD-2 1.5% Dextrose | 346 | 5.2 (4.0 to 6.5) | 132 | 3.5 | 0.5 | 96 | 40
DIANEAL PD-2 2.5% Dextrose | 396 | 5.2 (4.0 to 6.5) | 132 | 3.5 | 0.5 | 96 | 40
DIANEAL PD-2 4.25% Dextrose | 485 | 5.2 (4.0 to 6.5) | 132 | 3.5 | 0.5 | 96 | 40
DIANEAL Low Calcium (2.5 mEq/L) 1.5% Dextrose | 344 | 5.2 (4.0 to 6.5) | 132 | 2.5 | 0.5 | 95 | 40
DIANEAL Low Calcium (2.5 mEq/L) 2.5% Dextrose | 395 | 5.2 (4.0 to 6.5) | 132 | 2.5 | 0.5 | 95 | 40
DIANEAL Low Calcium (2.5 mEq/L) 4.25% Dextrose | 483 | 5.2 (4.0 to 6.5) | 132 | 2.5 | 0.5 | 95 | 40

Table 2 - DIANEAL Low Calcium Peritoneal Dialysis Solution Plastic container with blue pull tip for APD therapy
 |  |  | Ionic Concentration (mEq/L)
 | OSMOLARITY (mOsmol/L) (calc) | pH | Sodium | Calcium | Magnesium | Chloride | Lactate
DIANEAL Low Calcium (2.5 mEq/L) 1.5% Dextrose | 344 | 5.0 to 6.5 | 132 | 2.5 | 0.5 | 95 | 40
DIANEAL Low Calcium (2.5 mEq/L) 2.5% Dextrose | 395 | 5.0 to 6.5 | 132 | 2.5 | 0.5 | 95 | 40
DIANEAL Low Calcium (2.5 mEq/L) 4.25% Dextrose | 483 | 5.0 to 6.5 | 132 | 2.5 | 0.5 | 95 | 40

Table 3 – DIANEAL PD-2 and DIANEAL Low Calcium Peritoneal Dialysis Solution Plastic container with pull ring for APD therapy
 | OSMOLARITY (mOsmol/L) (calc) | pH | Ionic Concentration (mEq/L)
 | OSMOLARITY (mOsmol/L) (calc) | pH | Sodium | Calcium | Magnesium | Chloride | Lactate
DIANEAL PD-2; 1.5% Dextrose | 346 | 5.0 to 5.6 | 132 | 3.5 | 0.5 | 96 | 40
DIANEAL PD-2; 2.5% Dextrose | 396 | 5.0 to 5.6 | 132 | 3.5 | 0.5 | 96 | 40
DIANEAL Low Calcium (2.5 mEq/L) 1.5% Dextrose | 344 | 5.0 to 5.6 | 132 | 2.5 | 0.5 | 95 | 40
DIANEAL Low Calcium (2.5 mEq/L) 2.5% Dextrose | 395 | 5.0 to 5.6 | 132 | 2.5 | 0.5 | 95 | 40

4 CONTRAINDICATIONS

DIANEAL peritoneal dialysis solutions are contraindicated in patients with severe lactic acidosis.

5 WARNINGS AND PRECAUTIONS

5.1 Peritonitis and Encapsulating Peritoneal Sclerosis

Peritonitis has been associated with DIANEAL peritoneal dialysis solution use. Following use, inspect the drained fluid for the presence of fibrin or cloudiness, which may indicate the presence of peritonitis. Improper clamping or priming sequence may result in infusion of air into the peritoneal cavity, which may result in abdominal pain and/or peritonitis. If peritonitis occurs, treat with appropriate therapy.

Encapsulating Peritoneal Sclerosis (EPS), sometimes fatal, is a complication of peritoneal dialysis therapy and has been reported in patients using DIANEAL solutions.

5.2 Lactic Acidosis

Monitor patients with conditions known to increase the risk of lactic acidosis [e.g., severe hypotension or sepsis that can be associated with acute renal failure, hepatic failure, inborn errors of metabolism, and treatment with drugs such as nucleoside/nucleotide reverse transcriptase inhibitors (NRTIs)] before the start of treatment and during treatment with lactate-based peritoneal dialysis solutions. Use of DIANEAL solutions in patients with severe lactic acidosis is contraindicated [see Contraindications (4)].

5.3 Overinfusion

Overinfusion of peritoneal dialysis solution volume into the peritoneal cavity may be characterized by abdominal distention, feeling of fullness and/or shortness of breath. Drain the peritoneal dialysis solution from the peritoneal cavity to treat overinfusion.

5.4 Electrolyte, Fluid, and Nutrition Imbalances

Peritoneal dialysis may affect a patient’s protein, water-soluble vitamin, potassium, bicarbonate, calcium, and magnesium levels and volume status. Monitor hematology, electrolytes, blood chemistry and fluid status periodically and take appropriate clinical action.

Potassium is omitted from DIANEAL solutions because dialysis may be performed to correct hyperkalemia. In situations where there is a normal serum potassium level or hypokalemia, addition of potassium chloride (up to a concentration of 4 mEq/L) to the solution may be necessary to prevent severe hypokalemia. Monitor fluid status to avoid hyper- or hypovolemia and potentially severe consequences including congestive heart failure, volume depletion and hypovolemic shock.

5.5 Hyperglycemia

DIANEAL solutions contain dextrose and may increase the risk for hyperglycemia in patients with impaired glucose tolerance. Patients may require initiation or modification of antidiabetic therapy during treatment with DIANEAL solutions. Monitor blood glucose.

6 ADVERSE REACTIONS

The following adverse reactions are discussed elsewhere in the label:

Peritonitis and Encapsulating Peritoneal Sclerosis [see Warnings and Precautions (5.1)]

Electrolyte and Fluid Imbalances [see Warnings and Precautions (5.4)]

6.1 Clinical Trials Experience

There are no data available on adverse reactions from controlled clinical trials conducted to evaluate the safety of DIANEAL peritoneal dialysis solutions.

6.2 Post-Marketing Experience

The following adverse experiences have been identified during post-approval use of DIANEAL solutions or in conjunction with performing the peritoneal dialysis procedure. Because these experiences are reported voluntarily from a population of uncertain size, it is not always possible to reliably estimate their frequency or establish a causal relationship during drug exposure. Most of these adverse experiences are believed to be consequences of peritoneal dialysis.

INFECTIONS AND INFESTATIONS: Fungal peritonitis, Peritonitis bacterial, Catheter related infection

METABOLISM AND NUTRITION DISORDERS: Hypovolemia, Hypervolemia, Fluid retention, Hypokalemia, Hyponatremia, Dehydration, Hypochloremia

VASCULAR DISORDERS: Hypotension, Hypertension

RESPIRATORY, THORACIC, AND MEDIASTINAL DISORDERS: Dyspnea

GASTROINTESTINAL DISORDERS: Sclerosing encapsulating peritonitis, Peritonitis, Peritoneal cloudy effluent, Vomiting, Diarrhea, Nausea, Constipation, Abdominal pain, Abdominal distension, Abdominal discomfort

SKIN AND SUBCUTANEOUS DISORDERS: Stevens-Johnson syndrome, Urticaria, Rash, (including pruritic, erythematous and generalized), Pruritus

MUSCULOSKELETAL, CONNECTIVE TISSUE DISORDERS: Myalgia, Muscle spasms, Musculoskeletal pain

GENERAL DISORDERS AND ADMINISTRATION SITE CONDITIONS: Generalized edema, Pyrexia, Malaise, Infusion site pain, Catheter related complication

7 DRUG INTERACTIONS

As with other dialysis solutions, blood concentrations of dialyzable drugs may be reduced by dialysis. Dosage adjustment of concomitant medications may be necessary.

Diabetic patients may require dosage adjustments of insulin or other treatments for hyperglycemia [see Warnings and Precautions (5.5)].

8 USE IN SPECIFIC POPULATIONS

8.1 Pregnancy

DIANEAL peritoneal dialysis solution is a pharmacologically inactive solution. While there are no adequate and well controlled studies in pregnant women, appropriate administration of DIANEAL solutions, with appropriate monitoring of hematology, electrolytes, blood chemistry and fluid status is not expected to cause fetal harm. Animal reproduction studies have not been conducted with DIANEAL solutions.

The estimated background risk of major birth defects and miscarriage for the indicated population is unknown. In the U.S. general population, the estimated background risk of major birth defects and miscarriage in clinically recognized pregnancies is 2-4% and 15-20%, respectively.

8.2 Lactation

The components of DIANEAL solutions are excreted in human milk.

8.4 Pediatric Use

Safety and effectiveness have been established based on published clinical data. No adequate and well-controlled studies have been conducted with DIANEAL solutions in pediatric patients.

8.5 Geriatric Use

Safety and effectiveness have been established based on published clinical data.

10 OVERDOSAGE

There is a potential for overdose resulting in hypervolemia, hypovolemia, electrolyte disturbances or hyperglycemia. Excessive use of DIANEAL peritoneal dialysis solution with 4.25% dextrose during a peritoneal dialysis treatment can result in significant removal of water from the patient.

11 DESCRIPTION

DIANEAL peritoneal dialysis solutions are sterile, nonpyrogenic solutions in flexible containers for intraperitoneal administration only. The peritoneal dialysis solutions contain no bacteriostatic or antimicrobial agents.

DIANEAL solutions are hyperosmolar solutions.

Table 4 - DIANEAL PD-2 and Low Calcium Peritoneal Dialysis Solution ULTRABAG Container for CAPD therapy AMBU-FLEX/Plastic Container with pull ring for APD therapy
 | Composition/100 mL
 | *Dextrose, Hydrous, USP | Sodium Chloride, USP (NaCl) | Sodium Lactate (C3H5NaO3) | Calcium Chloride, USP (CaCl2•2H2O) | Magnesium Chloride, USP (MgCl2•6H2O)
DIANEAL PD-2 1.5% Dextrose | 1.5 g | 538 mg | 448 mg | 25.7 mg | 5.08 mg
DIANEAL PD-2 2.5% Dextrose | 2.5 g | 538 mg | 448 mg | 25.7 mg | 5.08 mg
DIANEAL PD-2 4.25% Dextrose | 4.25 g | 538 mg | 448 mg | 25.7 mg | 5.08 mg
DIANEAL Low Calcium (2.5 mEq/L) 1.5% Dextrose | 1.5 g | 538 mg | 448 mg | 18.3 mg | 5.08 mg
DIANEAL Low Calcium (2.5 mEq/L) 2.5% Dextrose | 2.5 g | 538 mg | 448 mg | 18.3 mg | 5.08 mg
DIANEAL Low Calcium (2.5 mEq/L) 4.25% Dextrose | 4.25 g | 538 mg | 448 mg | 18.3 mg | 5.08 mg

Table 5 - DIANEAL Low Calcium Peritoneal Dialysis Solution Plastic container with blue pull tip for APD therapy
 | Composition/100 mL
 | *Dextrose, Hydrous | Sodium Chloride (NaCl) | Sodium Lactate (C3H5NaO3) | Calcium Chloride (CaCl2•2H2O) | Magnesium Chloride (MgCl2•6H2O)
DIANEAL Low Calcium (2.5 mEq/L) 1.5% Dextrose | 1.5 g | 538 mg | 448 mg | 18.4 mg | 5.08 mg
DIANEAL Low Calcium (2.5 mEq/L) 2.5% Dextrose | 2.5 g | 538 mg | 448 mg | 18.4 mg | 5.08 mg
DIANEAL Low Calcium (2.5 mEq/L) 4.25% Dextrose | 4.25 g | 538 mg | 448 mg | 18.4 mg | 5.08 mg

The plastic container is fabricated from polyvinyl chloride (PVC Plastic). Exposure to temperatures above 25°C/77°F during transport and storage will lead to minor losses in moisture content. Higher temperatures lead to greater losses. It is unlikely that these minor losses will lead to clinically significant changes within the expiration period. The amount of water that can permeate from inside the solution container into the overwrap is insufficient to affect the solution significantly.

Solutions in contact with the plastic container can leach out certain of its chemical components in very small amounts within the expiration period, e.g. di-2-ethylhexyl phthalate (DEHP), up to 5 parts per million; however, the safety of the plastic has been confirmed in tests in animals according to USP biological tests for plastic containers as well as by cell culture toxicity studies.

12 CLINICAL PHARMACOLOGY

12.1 Mechanism of Action

DIANEAL peritoneal dialysis solutions are a pharmacologically inactive, hypertonic peritoneal dialysis solution containing dextrose, a monosaccharide, as the primary osmotic agent. An osmotic gradient must be created between the peritoneal membrane and the dialysis solution in order for ultrafiltration to occur. The hypertonic concentration of glucose in DIANEAL solutions exert an osmotic pressure across the peritoneal membrane resulting in transcapillary ultrafiltration. Like other peritoneal dialysis solutions, DIANEAL solutions contain electrolytes to facilitate the correction of electrolyte abnormalities. DIANEAL solutions contain a buffer, lactate, to help normalize acid-base abnormalities.

12.3 Pharmacokinetics

Absorption

Glucose is rapidly absorbed from the peritoneal cavity by diffusion and appears quickly in the circulation due to the high glucose concentration gradient between DIANEAL solutions compared to blood capillary glucose level. Absorption per unit time will be the highest at the start of an exchange and decreases over time. The rate of glucose absorption will be dependent upon the transport characteristics of the patient’s peritoneal membrane as determined by a peritoneal equilibration test (PET). Glucose absorption will also depend upon the concentration of glucose used for the exchange and the length of the dwell. Transport of other molecules will be dependent upon the molecular size of the solute, the concentration gradient, and the effective peritoneal surface area as determined by the PET.

Metabolism and Elimination

Glucose is metabolized by normal cellular pathways (i.e., glycolysis). Metabolism of lactate occurs in the liver and results in the generation of the bicarbonate. Glucose not absorbed during PD exchange procedure is removed by drainage of the PD solution from the peritoneal cavity.

Drug Interaction Studies

Heparin

No human drug interaction studies with heparin were conducted. In vitro studies demonstrated no evidence of incompatibility of heparin with DIANEAL solutions.

Antibiotics

No formal clinical drug interaction studies have been performed. In vitro studies of the following medications have demonstrated stability with DIANEAL solutions: amphotericin B, ampicillin, cefazolin, cefepime, cefotaxime, ceftazidime, ceftriaxone, ciprofloxacin, clindamycin, deferoxamine, erythromycin, gentamicin, linezolid, mezlocillin, miconazole, moxifloxacin, nafcillin, ofloxacin, penicillin G, piperacillin, sulfamethoxazole/trimethoprim, ticarcillin, tobramycin, and vancomycin. However, aminoglycosides should not be mixed with penicillins due to chemical incompatibility.

16 HOW SUPPLIED/STORAGE AND HANDLING

DIANEAL peritoneal dialysis solutions are available in the following single-dose containers and fill volumes as shown in Tables 6-7:

Table 6 - DIANEAL Peritoneal Dialysis Solutions for CAPD therapy
Container | Fill Volume (mL) | Container Size (mL) | Product Code | NDC
ULTRABAG Container | DIANEAL PD-2 Peritoneal Dialysis Solution with 1.5% Dextrose
ULTRABAG Container | 2000; 2500 | 2000; 3000 | 5B9866; 5B9868 | 0941-0426-52; 0941-0426-53
ULTRABAG Container | DIANEAL PD-2 Peritoneal Dialysis Solution with 2.5% Dextrose
ULTRABAG Container | 2000; 2500 | 2000; 3000 | 5B9876; 5B9878 | 0941-0427-52; 0941-0427-53
ULTRABAG Container | DIANEAL PD-2 Peritoneal Dialysis Solution with 4.25% Dextrose
ULTRABAG Container | 2000; 2500 | 2000; 3000 | 5B9896; 5B9898 | 0941-0429-52; 0941-0429-53
ULTRABAG Container | DIANEAL Low Calcium (2.5 mEq/L) Peritoneal Dialysis Solution with 1.5% Dextrose
ULTRABAG Container | 1500; 2000; 2500 | 2000; 2000; 3000 | 5B9765; 5B9766; 5B9768 | 0941-0424-51; 0941-0424-52; 0941-0424-53
ULTRABAG Container | DIANEAL Low Calcium (2.5 mEq/L) Peritoneal Dialysis Solution with 2.5% Dextrose
ULTRABAG Container | 1500; 2000; 2500 | 2000; 2000; 3000 | 5B9775; 5B9776; 5B9778 | 0941-0430-51; 0941-0430-52; 0941-0430-53
ULTRABAG Container | DIANEAL Low Calcium (2.5 mEq/L) Peritoneal Dialysis Solution with 4.25% Dextrose
ULTRABAG Container | 1500; 2000; 2500 | 2000; 2000; 3000 | 5B9795; 5B9796; 5B9798 | 0941-0433-51; 0941-0433-52; 0941-0433-53

Table 7 - DIANEAL Peritoneal Dialysis Solutions for APD therapy
Container | Fill Volume (mL) | Container Size (mL) | Product Code | NDC
AMBU-FLEX / Plastic Container with pull ring | DIANEAL PD-2 Peritoneal Dialysis Solution with 1.5% Dextrose
AMBU-FLEX / Plastic Container with pull ring | 1000; 2000; 3000; 5000; 6000 | 1000; 3000; 3000; 6000; 6000 | L5B5163; L5B5166; L5B5169; L5B5193; L5B9710 | 0941-0411-05; 0941-0411-06; 0941-0411-04; 0941-0411-07; 0941-0411-11
AMBU-FLEX / Plastic Container with pull ring | DIANEAL PD-2 Peritoneal Dialysis Solution with 2.5% Dextrose
AMBU-FLEX / Plastic Container with pull ring | 1000; 2000; 3000; 5000; 6000 | 1000; 3000; 3000; 6000; 6000 | L5B5173; L5B5177; L5B5179; L5B5194; L5B9711 | 0941-0413-05; 0941-0413-06; 0941-0413-04; 0941-0413-07; 0941-0413-01
AMBU-FLEX / Plastic Container with pull ring | DIANEAL PD-2 Peritoneal Dialysis Solution with 4.25% Dextrose
AMBU-FLEX / Plastic Container with pull ring | 1000; 2000; 3000; 5000; 6000 | 1000; 3000; 3000; 6000; 6000 | L5B5183; L5B5187; L5B5189; L5B5195; L5B9712 | 0941-0415-05; 0941-0415-06; 0941-0415-04; 0941-0415-07; 0941-0415-01
AMBU-FLEX / Plastic Container with pull ring | DIANEAL Low Calcium (2.5 mEq/L) Peritoneal Dialysis Solution with 1.5%Dextrose
AMBU-FLEX / Plastic Container with pull ring | 2000; 3000; 5000; 6000 | 3000; 3000; 6000; 6000 | L5B4825; L5B9901; L5B4826; L5B9770 | 0941-0409-06; 0941-0409-05; 0941-0409-07; 0941-0409-01
AMBU-FLEX / Plastic Container with pull ring | DIANEAL Low Calcium (2.5 mEq/L) Peritoneal Dialysis Solution with 2.5% Dextrose
AMBU-FLEX / Plastic Container with pull ring | 2000; 3000; 5000; 6000 | 3000; 3000; 6000; 6000 | L5B9727; L5B9902; L5B5202; L5B9771 | 0941-0457-08; 0941-0457-02; 0941-0457-05; 0941-0457-01
AMBU-FLEX / Plastic Container with pull ring | DIANEAL Low Calcium (2.5 mEq/L) Peritoneal Dialysis Solution with 4.25% Dextrose
AMBU-FLEX / Plastic Container with pull ring | 2000; 3000; 5000; 6000 | 3000; 3000; 6000; 6000 | L5B9747; L5B9903; L5B5203; L5B9772 | 0941-0459-08; 0941-0459-02; 0941-0459-05; 0941-0459-01
Plastic container with blue pull tip | DIANEAL Low Calcium (2.5 mEq/L) Peritoneal Dialysis Solution with 1.5% Dextrose
Plastic container with blue pull tip | 5000 | 5000 | EZPB5245R | 0941-0484-01
Plastic container with blue pull tip | DIANEAL Low Calcium (2.5 mEq/L) Peritoneal Dialysis Solution with 2.5% Dextrose
Plastic container with blue pull tip | 5000 | 5000 | EZPB5255R | 0941-0487-01
Plastic container with blue pull tip | DIANEAL Low Calcium (2.5 mEq/L) Peritoneal Dialysis Solution with 4.25% Dextrose
Plastic container with blue pull tip | 5000 | 5000 | EZPB5265R | 0941-0490-01

All DIANEAL peritoneal dialysis solutions have overfills which are declared on container labeling.

Freezing of solution may occur at temperatures below 0°C (32°F). Allow to thaw naturally in ambient conditions and thoroughly mix contents by shaking.

Exposure of pharmaceutical products to heat should be minimized. Avoid excessive heat. It is recommended the product be stored at room temperature (25°C/77°F): brief exposure up to 40°C (104°F) does not adversely affect the product.

Store in moisture barrier overwrap and in carton until ready to use.

17 PATIENT COUNSELING INFORMATION

Inspection: Advise patients to inspect DIANEAL peritoneal dialysis solutions before use, and not to use if the solution is cloudy, discolored, contains particulate matter or if there is evidence of leakage.

Administration: Advise patients on proper administration and the importance of using aseptic technique throughout the entire PD procedure. Advise patients only to use dry heat to warm solution to about 37°C (98°F) and not to microwave or submerge in water.

Peritonitis: Advise patients to seek medical attention if they experience signs or symptoms of peritonitis.

Vantive, Ambu-Flex, Dianeal, MiniCap and UltraBag are trademarks of Vantive Health LLC or its affiliates.

Vantive US Healthcare LLC
Deerfield, IL 60015 USA
Printed in USA

0719010126

PACKAGE/LABEL PRINCIPAL DISPLAY PANEL

NDC 0941-0411-11 (07-25-00-0740) Container Label

L5B9710 6000 mL
NDC 0941-0411-11(APPROX 225 mL EXCESS)

Vantive Logo

Dianeal PD-2
Peritoneal Dialysis Solution
with 1.5% Dextrose

EACH 100 mL CONTAINS 1.5 g DEXTROSE
HYDROUS USP 538 mg SODIUM CHLORIDE
USP 448 mg SODIUM LACTATE
25.7 mg CALCIUM CHLORIDE USP 5.08 mg
MAGNESIUM CHLORIDE USP pH 5.2 (4.0 TO
6.5)

mEq/L SODIUM - 132 CALCIUM - 3.5
MAGNESIUM - 0.5 CHLORIDE - 96
LACTATE - 40 OSMOLARITY - 346 mOsmol/L
(CALC)

STERILE NONPYROGENIC

POTASSIUM CHLORIDE TO BE ADDED ONLY
UNDER THE DIRECTION OF A PHYSICIAN

SEE PACKAGE INSERT FOR DOSAGE INFORMATION

USE AS DIRECTED BY PHYSICIAN

FOR INTRAPERITONEAL ADMINISTRATION ONLY

CAUTIONS SQUEEZE AND INSPECT INNER BAG
WHICH MAINTAINS PRODUCT STERILITY DISCARD IF
LEAKS ARE FOUND

DO NOT USE UNLESS SOLUTION IS CLEAR

DISCARD UNUSED PORTION

Rx ONLY

STORE UNIT IN MOISTURE BARRIER OVERWRAP AT
ROOM TEMPERATURE (25°C/77°F) UNTIL READY
TO USE
AVOID EXCESSIVE HEAT SEE INSERT

Ambu-Flex II CONTAINER

VANTIVE US HEALTHCARE LLC
DEERFIELD IL 60015 USA

MADE IN USA

PD-2 1.5% Dextrose

Bar Code
(01)00309410411117

NDC 0941-0413-07 (07-25-00-0677) Container Label

L5B5194 5000 mL
NDC 0941-0413-07 (APPROX 150 mL EXCESS)

Vantive Logo

Dianeal PD-2
Peritoneal Dialysis Solution
with 2.5% Dextrose

EACH 100 mL CONTAINS 2.5 g DEXTROSE HYDROUS USP
538 mg SODIUM CHLORIDE USP 448 mg SODIUM LACTATE
25.7 mg CALCIUM CHLORIDE USP 5.08 mg MAGNESIUM
CHLORIDE USP pH 5.2 (4.0 TO 6.5)

mEq/L SODIUM - 132 CALCIUM - 3.5
MAGNESIUM - 0.5
CHLORIDE - 96 LACTATE - 40
OSMOLARITY - 396 mOsmol/L (CALC)

STERILE NONPYROGENIC

POTASSIUM CHLORIDE TO BE ADDED
ONLY UNDER THE DIRECTION OF A
PHYSICIAN

SEE PACKAGE INSERT FOR DOSAGE INFORMATION

USE AS DIRECTED BY PHYSICIAN

FOR INTRAPERITONEAL
ADMINISTRATION ONLY

CAUTIONS SQUEEZE AND INSPECT INNER BAG
WHICH MAINTAINS PRODUCT STERILITY
DISCARD IF LEAKS ARE FOUND

DO NOT USE UNLESS SOLUTION IS CLEAR

DISCARD UNUSED PORTION

Rx ONLY

STORE UNIT IN MOISTURE BARRIER OVERWRAP AT
ROOM TEMPERATURE (25°C/77°F) UNTIL READY TO
USE AVOID EXCESSIVE HEAT SEE INSERT

Ambu-Flex II CONTAINER

VANTIVE US HEALTHCARE LLC
DEERFIELD IL 60015 USA

MADE IN USA

PD-2 2.5% Dextrose

Bar Code
(01) 00309410413074

NDC 0941-0415-06 (07-25-56-591) Container Label

L5B5187 2000 mL
NDC 0941-0415-06 (APPROX 80 mL EXCESS)
3000 mL NOMINAL SIZE CONTAINER

Vantive Logo

Dianeal PD-2
Peritoneal Dialysis Solution
with 4.25% Dextrose

EACH 100 mL CONTAINS 4.25 g DEXTROSE HYDROUS USP
538 mg SODIUM CHLORIDE USP 448 mg SODIUM LACTATE
25.7 mg CALCIUM CHLORIDE USP 5.08 mg MAGNESIUM
CHLORIDE USP pH 5.2 (4.0 TO 6.5)

mEq/L SODIUM - 132 CALCIUM - 3.5 MAGNESIUM - 0.5
CHLORIDE - 96 LACTATE - 40
OSMOLARITY - 346 mOsmol/L (CALC)

STERILE NONPYROGENIC

POTASSIUM CHLORIDE TO BE ADDED ONLY UNDER
THE DIRECTION OF A PHYSICIAN

SEE PACKAGE INSERT FOR DOSAGE INFORMATION

USE AS DIRECTED BY PHYSICIAN

FOR INTRAPERITONEAL ADMINISTRATION ONLY

WARNING EXTENSIVE USE OF THIS SOLUTION
DURING ONE PERITONEAL DIALYSIS PROCEDURE CAN
RESULT IN SIGNIFICANT REMOVAL OF WATER FROM
THE PATIENT

CAUTIONS SQUEEZE AND INSPECT INNER BAG
WHICH MAINTAINS PRODUCT STERILITY DISCARD IF
LEAKS ARE FOUND

DO NOT USE UNLESS SOLUTION IS CLEAR

DISCARD UNUSED PORTION

Rx ONLY

STORE UNIT IN MOISTURE BARRIER OVERWRAP AT
ROOM TEMPERATURE (25°C/77°F) UNTIL READY TO
USE
AVOID EXCESSIVE HEAT SEE INSERT

Ambu-Flex II CONTAINER

VANTIVE US HEALTHCARE LLC
DEERFIELD IL 60015 USA

MADE IN USA

PD-2 4.25% Dextrose

NDC 0941-0409-07 (07-25-00-0676) Container Label

L5B4826 5000 mL
NDC 0941-0409-07 (APPROX 150 mL EXCESS)

Vantive Logo

Dianeal
Low Calcium (2.5 mEq/L)
Peritoneal Dialysis Solution
with 1.5% Dextrose

EACH 100 mL CONTAINS 1.5 g DEXTROSE HYDROUS USP
538 mg SODIUM CHLORIDE USP 448 mg SODIUM LACTATE
18.3 mg CALCIUM CHLORIDE USP 5.08 mg MAGNESIUM
CHLORIDE USP pH 5.2 (4.0 TO 6.5)

mEq/L SODIUM - 132 CALCIUM - 2.5
MAGNESIUM - 0.5
CHLORIDE - 95 LACTATE - 40
OSMOLARITY - 344 mOsmol/L (CALC)

STERILE NONPYROGENIC

POTASSIUM CHLORIDE TO BE ADDED ONLY
UNDER THE DIRECTION OF A PHYSICIAN

SEE PACKAGE INSERT FOR DOSAGE INFORMATION

USE AS DIRECTED BY PHYSICIAN

FOR INTRAPERITONEAL
ADMINISTRATION ONLY

CAUTIONS SQUEEZE AND INSPECT INNER BAG
WHICH MAINTAINS PRODUCT STERILITY
DISCARD IF LEAKS ARE FOUND

DO NOT USE UNLESS SOLUTION IS CLEAR

DISCARD UNUSED PORTION

Rx ONLY

STORE UNIT IN MOISTURE BARRIER OVERWRAP
AT ROOM TEMPERATURE (25°C/77°F) UNTIL READY
TO USE AVOID EXCESSIVE HEAT SEE INSERT

Ambu-Flex II CONTAINER

VANTIVE US HEALTHCARE LLC
DEERFIELD IL 60015 USA

MADE IN USA

Low Calcium 1.5% Dextrose

Bar Code
(01)00309410409077

NDC 0941-0457-08 (07-25-00-0739) Container Label

L5B9727 2000 mL
NDC 0941-0457-08 (APPROX 80 mL EXCESS)
3000 mL NOMINAL SIZE CONTANER

Vantive Logo

Dianeal
Low Calcium (2.5 mEq/L)
Peritoneal Dialysis Solution
with 2.5% Dextrose

EACH 100 mL CONTAINS 2.5 g DEXTROSE
HYDROUS USP 538 mg SODIUM CHLORIDE
USP 448 mg SODIUM LACTATE 18.3 mg
CALCIUM CHLORIDE USP 5.08 mg MAGNESIUM
CHLORIDE USP pH 5.2 (4.0 TO 6.5)

mEq/L SODIUM - 132 CALCIUM - 2.5
MAGNESIUM - 0.5 CHLORIDE - 95
LACTATE – 40 OSMOLARITY - 346 mOsmol/L
(CALC)

STERILE NONPYROGENIC

POTASSIUM CHLORIDE TO BE ADDED ONLY
UNDER THE DIRECTION OF A PHYSICIAN

SEE PACKAGE INSERT FOR DOSAGE
INFORMATION

USE AS DIRECTED BY PHYSICIAN

FOR INTRAPERITONEAL ADMINISTRATION ONLY

CAUTIONS SQUEEZE AND INSPECT INNER BAG
WHICH MAINTAINS PRODUCT STERILITY
DISCARD IF LEAKS ARE FOUND

DO NOT USE UNLESS SOLUTION IS CLEAR

DISCARD UNUSED PORTION

Rx ONLY

STORE UNIT IN MOISTURE BARRIER OVERWRAP AT
ROOM TEMPERATURE (25°C/77°F) UNTIL READY TO
USE AVOID EXCESSIVE HEAT SEE INSERT

Ambu-Flex II CONTAINER

VANTIVE US HEALTHCARE LLC
DEERFIELD IL 60015 USA

MADE IN USA

Low Calcium 2.5% Dextrose

Bar Code
(01)00309410457085

NDC 0941-0459-08 Container Label

L5B9747 2000 mL
NDC 0941-0459-08 (APPROX 80 mL EXCESS)
3000 mL NOMINAL SIZE CONTANER

Vantive Logo

Dianeal
Low Calcium (2.5 mEq/L)
Peritoneal Dialysis Solution
with 4.25% Dextrose

EACH 100 mL CONTAINS 4.25 g DEXTROSE HYDROUS USP
538 mg SODIUM CHLORIDE USP 448 mg SODIUM LACTATE
18.3 mg CALCIUM CHLORIDE USP 5.08 mg MAGNESIUM
CHLORIDE USP pH 5.2 (4.0 TO 6.5)

mEq/L SODIUM - 132 CALCIUM - 2.5 MAGNESIUM - 0.5
CHLORIDE - 95 LACTATE - 40
OSMOLARITY - 346 mOsmol/L (CALC)

STERILE NONPYROGENIC

POTASSIUM CHLORIDE TO BE ADDED ONLY UNDER
THE DIRECTION OF A PHYSICIAN

SEE PACKAGE INSERT FOR DOSAGE INFORMATION

USE AS DIRECTED BY PHYSICIAN

FOR INTRAPERITONEAL ADMINISTRATION ONLY

CAUTIONS SQUEEZE AND INSPECT INNER BAG
WHICH MAINTAINS PRODUCT STERILITY DISCARD IF
LEAKS ARE FOUND

DO NOT USE UNLESS SOLUTION IS CLEAR

DISCARD UNUSED PORTION

Rx ONLY

STORE UNIT IN MOISTURE BARRIER OVERWRAP AT
ROOM TEMPERATURE (25°C/77°F) UNTIL READY TO
USE
AVOID EXCESSIVE HEAT SEE INSERT

Ambu-Flex II CONTAINER PL 146 PLASTIC

VANTIVE US HEALTHCARE LLC
DEERFIELD IL 60015 USA

MADE IN USA

Low Calcium 4.25% Dextrose

NDC 0941-0426-52 Container Label

5B9866 2000 mL
NDC 0941-0426-52 (APPROX 80 mL EXCESS)

Vantive Logo

Dianeal PD-2
Peritoneal Dialysis Solution
with 1.5% Dextrose

EACH 100 mL CONTAINS 1.5 g DEXTROSE HYDROUS USP
538 mg SODIUM CHLORIDE USP 448 mg SODIUM
LACTATE 25.7 mg CALCIUM CHLORIDE USP 5.08 mg
MAGNESIUM CHLORIDE USP pH 5.2 (4.0 TO 6.5)

mEq/L SODIUM - 132 CALCIUM - 3.5 MAGNESIUM - 0.5
CHLORIDE - 96 LACTATE - 40
OSMOLARITY - 346 mOsmol/L (CALC)

STERILE NONPYROGENIC

POTASSIUM CHLORIDE TO BE ADDED ONLY
UNDER THE DIRECTION OF A PHYSICIAN

READ PACKAGE INSERT FOR FULL INFORMATION

FOR INTRAPERITONEAL ADMINISTRATION ONLY

DOSAGE AS DIRECTED BY PHYSICIAN

CAUTIONS SQUEEZE AND INSPECT INNER BAG
WHICH MAINTAINS PRODUCT STERILITY DISCARD
IF LEAKS ARE FOUND

DO NOT USE UNLESS SOLUTION IS CLEAR

DISCARD UNUSED PORTION

Rx ONLY

STORE UNIT IN MOISTURE BARRIER OVERWRAP AT
ROOM TEMPERATURE (25°C/77°F) UNTIL READY TO
USE AVOID EXCESSIVE HEAT SEE INSERT

UltraBag CONTAINER

VANTIVE US HEALTHCARE LLC
DEERFIELD IL 60015 USA

MADE IN USA

PD-2 1.5% Dextrose

NDC 0941-0427-52 Container Label

5B9876 2000 mL
NDC 0941-0427-52 (APPROX 80 mL EXCESS)

Vantive Logo

Dianeal PD-2
Peritoneal Dialysis Solution
with 2.5% Dextrose

EACH 100 mL CONTAINS 2.5 g DEXTROSE HYDROUS USP
538 mg SODIUM CHLORIDE USP 448 mg SODIUM
LACTATE 25.7 mg CALCIUM CHLORIDE USP 5.08 mg
MAGNESIUM CHLORIDE USP pH 5.2 (4.0 TO 6.5)

mEq/L SODIUM - 132 CALCIUM - 3.5 MAGNESIUM - 0.5
CHLORIDE - 96 LACTATE - 40
OSMOLARITY - 346 mOsmol/L (CALC)

STERILE NONPYROGENIC

POTASSIUM CHLORIDE TO BE ADDED ONLY UNDER
THE DIRECTION OF A PHYSICIAN

READ PACKAGE INSERT FOR FULL INFORMATION

FOR INTRAPERITONEAL ADMINISTRATION ONLY

DOSAGE AS DIRECTED BY PHYSICIAN

CAUTIONS SQUEEZE AND INSPECT INNER BAG
WHICH MAINTAINS PRODUCT STERILITY DISCARD
IF LEAKS ARE FOUND

DO NOT USE UNLESS SOLUTION IS CLEAR

DISCARD UNUSED PORTION

Rx ONLY

STORE UNIT IN MOISTURE BARRIER OVERWRAP
AT ROOM TEMPERATURE (25°C/77°F) UNTIL
READY TO USE

AVOID EXCESSIVE HEAT SEE INSERT

UltraBag CCONTAINER

VANTIVE US HEALTHCARE LLC
DEERFIELD IL 60015 USA

MADE IN USA

PD-2 2.5% Dextrose

NDC 0941-0429-52 Container Label

5B9896 2000 mL
NDC 0941-0429-52 (APPROX 80 mL EXCESS)

Vantive Logo

Dianeal PD-2
Peritoneal Dialysis Solution
with 4.25% Dextrose

EACH 100 mL CONTAINS 4.25 g DEXTROSE HYDROUS USP
538 mg SODIUM CHLORIDE USP 448 mg SODIUM LACTATE
25.7 mg CALCIUM CHLORIDE USP 5.08 mg MAGNESIUM
CHLORIDE USP pH 5.2 (4.0 TO 6.5)

mEq/L SODIUM - 132 CALCIUM - 3.5 MAGNESIUM - 0.5
CHLORIDE - 96 LACTATE - 40
OSMOLARITY - 346 mOsmol/L (CALC)

STERILE NONPYROGENIC

POTASSIUM CHLORIDE TO BE ADDED ONLY
UNDER THE DIRECTION OF A PHYSICIAN

READ PACKAGE INSERT FOR FULL INFORMATION

WARNING EXTENSIVE USE OF THIS SOLUTION DURING
ONE PERITONEAL DIALYSIS PROCEDURE CAN RESULT IN
SIGNIFICANT REMOVAL OF WATER FROM THE PATIENT

FOR INTRAPERITONEAL ADMINISTRATION ONLY

DOSAGE AS DIRECTED BY A PHYSICIAN

CAUTIONS SQUEEZE AND INSPECT INNER BAG
WHICH MAINTAINS PRODUCT STERILITY DISCARD IF
LEAKS ARE FOUND

DO NOT USE UNLESS SOLUTION IS CLEAR

DISCARD UNUSED PORTION
Rx ONLY

STORE UNIT IN MOISTURE BARRIER OVERWRAP AT
ROOM TEMPERATURE (25°C/77°F) UNTIL READY TO
USE AVOID EXCESSIVE HEAT SEE INSERT

UltraBag CONTAINER

VANTIVE US HEALTHCARE LLC
DEERFIELD IL 60015 USA

MADE IN USA

PD-2 4.25% Dextrose

NDC 0941-0424-52 Container Label

5B9766 2000 mL
NDC 0941-0424-52 (APPROX 80 mL EXCESS)

Vantive Logo

Dianeal
Low Calcium (2.5 mEq/L) Peritoneal Dialysis Solution
with 1.5% Dextrose

EACH 100 mL CONTAINS 1.5 g DEXTROSE HYDROUS USP
538 mg SODIUM CHLORIDE USP 448 mg SODIUM
LACTATE 18.3 mg CALCIUM CHLORIDE USP 5.08 mg
MAGNESIUM CHLORIDE USP pH 5.2 (4.0 TO 6.5)

mEq/L SODIUM - 132 CALCIUM - 2.5
MAGNESIUM - 0.5
CHLORIDE - 95 LACTATE - 40
OSMOLARITY - 346 mOsmol/L (CALC)

STERILE NONPYROGENIC

POTASSIUM CHLORIDE TO BE ADDED ONLY
UNDER THE DIRECTION OF A PHYSICIAN

READ PACKAGE INSET FOR FULL
INFORMATION

FOR INTRAPERITONEAL
ADMINISTRATION ONLY

DOSAGE AS DIRECTED BY PHYSICIAN

CAUTIONS SQUEEZE AND INSPECT INNER BAG
WHICH MAINTAINS PRODUCT STERILITY
DISCARD IF LEAKS ARE FOUND

DO NOT USE UNLESS SOLUTION IS CLEAR

DISCARD UNUSED PORTION

Rx ONLY

STORE UNIT IN MOISTURE BARRIER OVERWRAP AT
ROOM TEMPERATURE (25°C/77°F) UNTIL READY TO
USE AVOID EXCESSIVE HEAT SEE INSERT

UltraBag CONTAINER

VANTIVE US HEALTHCARE LLC
DEERFIELD IL 60015 USA

MADE IN USA

Low Calcium 1.5% Dextrose

NDC 0941-0430-52 (07-25-00-0683) Container Label

5B9776 2000 mL
NDC 0941-0430-52 (APPROX 80 mL EXCESS)

Vantive Logo

Dianeal
Low Calcium (2.5 mEq/L) Peritoneal Dialysis Solution
with 2.5% Dextrose

EACH 100 mL CONTAINS 1.5 g DEXTROSE HYDROUS USP
538 mg SODIUM CHLORIDE USP 448 mg SODIUM LACTATE
18.3 mg CALCIUM CHLORIDE USP 5.08 mg MAGNESIUM
CHLORIDE USP pH 5.2 (4.0 TO 6.5)

mEq/L SODIUM - 132 CALCIUM - 2.5
MAGNESIUM - 0.5
CHLORIDE - 95 LACTATE - 40
OSMOLARITY - 346 mOsmol/L (CALC)

STERILE NONPYROGENIC

POTASSIUM CHLORIDE TO BE ADDED ONLY
UNDER THE DIRECTION OF A PHYSICIAN

READ PACKAGE INSET FOR FULL
INFORMATION

FOR INTRAPERITONEAL
ADMINISTRATION ONLY

DOSAGE AS DIRECTED BY PHYSICIAN

CAUTIONS SQUEEZE AND INSPECT INNER BAG
WHICH MAINTAINS PRODUCT STERILITY DISCARD
IF LEAKS ARE FOUND

DO NOT USE UNLESS SOLUTION IS CLEAR

DISCARD UNUSED PORTION

Rx ONLY

STORE UNIT IN MOISTURE BARRIER OVERWRAP AT
ROOM TEMPERATURE (25°C/77°F) UNTIL READY TO
USE AVOID EXCESSIVE HEAT SEE INSERT

UltraBag CONTAINER

VANTIVE US HEALTHCARE LLC
DEERFIELD IL 60015 USA

MADE IN USA

Low Calcium 2.5% Dextrose

NDC 0941-0433-52 Container Label

5B9796 2000 mL
NDC 0941-0433-52 (APPROX 80 mL EXCESS)

Vantive Logo

Dianeal
Low Calcium (2.5 mEq/L) Peritoneal Dialysis Solution
with 4.25% Dextrose

EACH 100 mL CONTAINS 4.25 g DEXTROSE HYDROUS USP
538 mg SODIUM CHLORIDE USP 448 mg SODIUM LACTATE
18.3 mg CALCIUM CHLORIDE USP 5.08 mg MAGNESIUM
CHLORIDE USP pH 5.2 (4.0 TO 6.5)

mEq/L SODIUM - 132 CALCIUM - 2.5 MAGNESIUM - 0.5
CHLORIDE - 95 LACTATE - 40
OSMOLARITY - 346 mOsmol/L (CALC)

STERILE NONPYROGENIC

POTASSIUM CHLORIDE TO BE ADDED ONLY
UNDER THE DIRECTION OF A PHYSICIAN

READ PACKAGE INSET FOR FULL INFORMATION

WARNING EXTENSIVE USE OF THIS SOLUTION DURING
ONE PERITONEAL DIALYSIS PROCEDURE CAN RESULT IN
SIGNIFICANT REMOVAL OF WATER FROM THE PATIENT

FOR INTRAPERITONEAL ADMINISTRATION ONLY

DOSAGE AS DIRECTED BY PHYSICIAN

CAUTIONS SQUEEZE AND INSPECT INNER BAG WHICH
MAINTAINS PRODUCT STERILITY DISCARD IF LEAKS
ARE FOUND

DO NOT USE UNLESS SOLUTION IS CLEAR

DISCARD UNUSED PORTION

Rx ONLY

STORE UNIT IN MOISTURE BARRIER OVERWRAP AT ROOM
TEMPERATURE (25°C/77°F) UNTIL READY TO USE
AVOID EXCESSIVE HEAT SEE INSERT

UltraBag CONTAINER

VANTIVE US HEALTHCARE LLC
DEERFIELD IL 60015 USA

MADE IN USA

Low Calcium 2.5% Dextrose

NDC 0941-0484-01 Container Label

LOT EXPIRY

EZPB5245R
NDC 0941-0484-01

5000 mL
(APPROX 135 mL EXCESS)

Vantive Logo

Dianeal
Low Calcium (2.5 mEq/L)
Peritoneal Dialysis Solution
with 1.5% Dextrose

Low Calcium 1.5% Dextrose

EACH 100 mL CONTAINS
448 mg SODIUM LACTATE
pH 5.0 to 6.5

1.5 g DEXTROSE HYDROUS
18.4 mg CALCIUM CHLORIDE

538 mg SODIUM CHLORIDE
5.08 mg MAGNESIUM CHLORIDE

mEq/L SODIUM – 132 CALCIUM – 2.5 MAGNESIUM – 0.5 CHLORIDE – 95 LACTATE – 40
OSMOLARITY – 344 mOsmol/L (CALC)

STERILE NONPYROGENIC

POTASSIUM CHLORIDE TO BE ADDED ONLY UNDER THE DIRECTION OF A PHYSICIAN

SEE PACKAGE INSERT FOR DOSAGE INFORMATION

USE AS DIRECTED BY PHYSICIAN

FOR INTRAPERITONEAL ADMINISTRATION ONLY

CAUTIONS SQUEEZE AND INSPECT INNER BAG WHICH
  MAINTAINS PRODUCT STERILITY DISCARD IF LEAKS ARE FOUND

DO NOT USE UNLESS SOLUTION IS CLEAR

DISCARD UNUSED PORTION

Rx ONLY

STORE UNIT IN MOISTURE BARRIER OVERWRAP AT ROOM TEMPERATURE (25°C/77°F) UNTIL READY
TO USE AVOID EXCESSIVE HEAT SEE INSERT
PLASTIC CONTAINER WITH BLUE PULL TIP

VANTIVE US HEALTHCARE LLC DEERFIELD IL 60015 USA

MADE IN IRELAND

CB-35-05-678

NDC 0941-0487-01 Container Label

LOT EXPIRY

EZPB5255R
NDC 0941-0487-01

5000 mL
(APPROX 135 mL EXCESS)

Vantive Logo

Dianeal
Low Calcium (2.5 mEq/L)
Peritoneal Dialysis Solution
with 2.5% Dextrose

Low Calcium 2.5% Dextrose

EACH 100 mL CONTAINS
448 mg SODIUM LACTATE
pH 5.0 to 6.5

2.5 g DEXTROSE HYDROUS
18.4 mg CALCIUM CHLORIDE

538 mg SODIUM CHLORIDE
5.08 mg MAGNESIUM CHLORIDE

mEq/L SODIUM – 132 CALCIUM – 2.5 MAGNESIUM – 0.5 CHLORIDE – 95 LACTATE – 40
OSMOLARITY – 395 mOsmol/L (CALC)

STERILE NONPYROGENIC

POTASSIUM CHLORIDE TO BE ADDED ONLY UNDER THE DIRECTION OF A PHYSICIAN

SEE PACKAGE INSERT FOR DOSAGE INFORMATION

USE AS DIRECTED BY PHYSICIAN

FOR INTRAPERITONEAL ADMINISTRATION ONLY

CAUTIONS SQUEEZE AND INSPECT INNER BAG WHICH MAINTAINS PRODUCT STERILITY DISCARD IF LEAKS ARE FOUND

DO NOT USE UNLESS SOLUTION IS CLEAR

DISCARD UNUSED PORTION

Rx ONLY

STORE UNIT IN MOISTURE BARRIER OVERWRAP AT ROOM TEMPERATURE (25ºC/77ºF) UNTIL READY TO USE AVOID EXCESSIVE HEAT SEE INSERT

PLASTIC CONTAINER WITH BLUE PULL TIP

VANTIVE US HEALTHCARE LLC DEERFIELD IL 60015 USA

MADE IN IRELAND

CB-35-05-676

NDC 0941-0490-01 Container Label

LOT EXPIRY

EZPB5265R
NDC 0941-0490-01

5000 mL
(APPROX 135 mL EXCESS)

Vantive Logo

Dianeal
Low Calcium (2.5 mEq/L)
Peritoneal Dialysis Solution
with 4.25% Dextrose

Low Calcium 4.25% Dextrose

EACH 100 mL CONTAINS
448 mg SODIUM LACTATE
pH 5.0 to 6.5

4.25 g DEXTROSE HYDROUS
18.4 mg CALCIUM CHLORIDE

538 mg SODIUM CHLORIDE
5.08 mg MAGNESIUM CHLORIDE

mEq/L SODIUM – 132 CALCIUM – 2.5 MAGNESIUM – 0.5 CHLORIDE – 95 LACTATE – 40
OSMOLARITY – 483 mOsmol/L (CALC)

STERILE NONPYROGENIC

POTASSIUM CHLORIDE TO BE ADDED ONLY UNDER THE DIRECTION OF A PHYSICIAN

SEE PACKAGE INSERT FOR DOSAGE INFORMATION

USE AS DIRECTED BY PHYSICIAN

FOR INTRAPERITONEAL ADMINISTRATION ONLY

WARNING EXTENSIVE USE OF THIS SOLUTION DURING ONE PERITONEAL DIALYSIS
PROCEDURE CAN RESULT IN SIGNIFICANT REMOVAL OF WATER FROM THE PATIENT

CAUTIONS SQUEEZE AND INSPECT INNER BAG WHICH MAINTAINS PRODUCT STERILITY DISCARD IF LEAKS ARE FOUND

DO NOT USE UNLESS SOLUTION IS CLEAR

DISCARD UNUSED PORTION

Rx ONLY

STORE UNIT IN MOISTURE BARRIER OVERWRAP AT ROOM TEMPERATURE (25ºC/77ºF) UNTIL READY
TO USE AVOID EXCESSIVE HEAT SEE INSERT

VANTIVE US HEALTHCARE LLC DEERFIELD IL 60015 USA

MADE IN IRELAND

CB-35-05-677